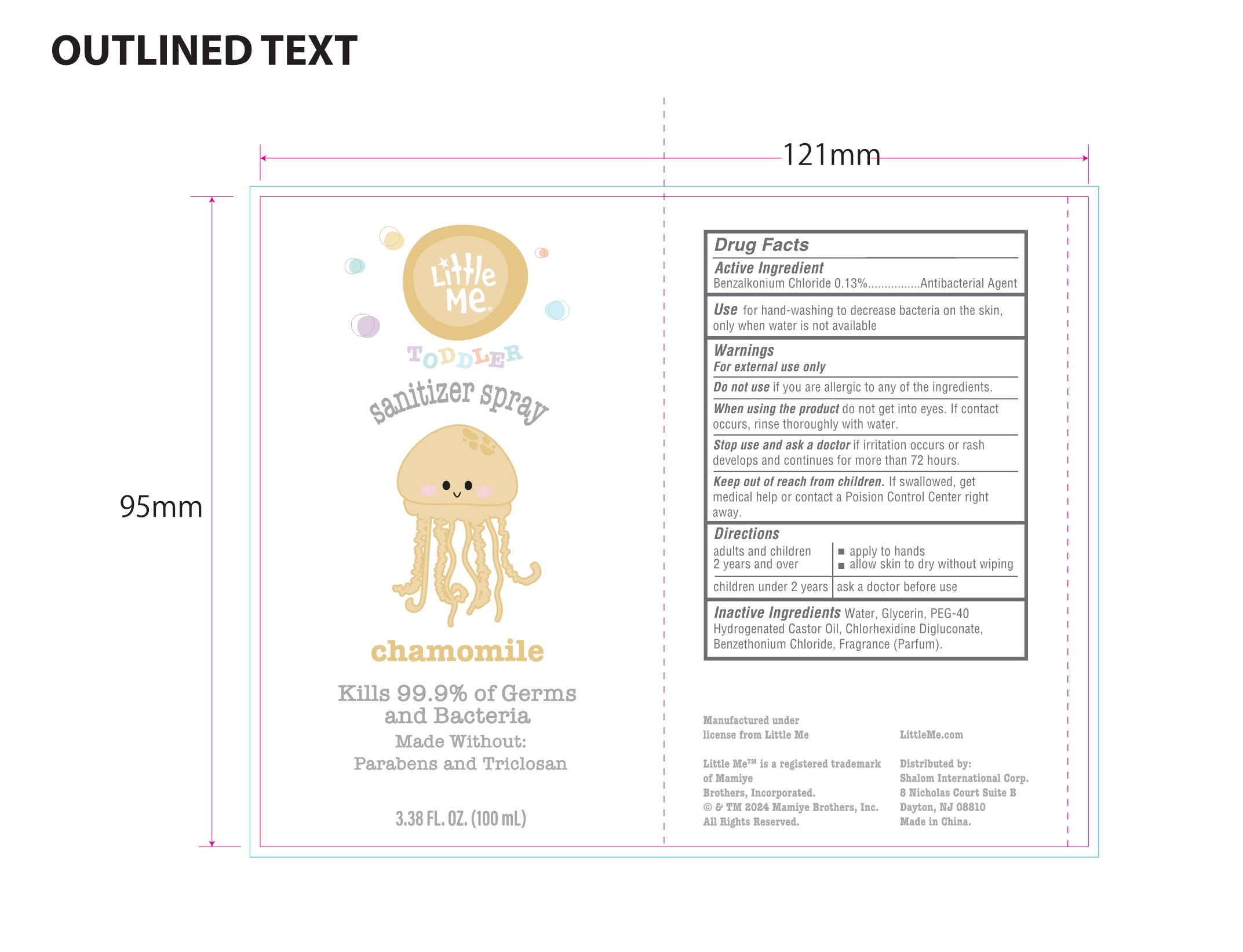 DRUG LABEL: Little Me Sanitizer
NDC: 76860-006 | Form: SPRAY
Manufacturer: Taizhou Huangyan Liweir Cosmetic Technology Ltd.
Category: otc | Type: HUMAN OTC DRUG LABEL
Date: 20240416

ACTIVE INGREDIENTS: BENZALKONIUM CHLORIDE 0.13 g/100 mL
INACTIVE INGREDIENTS: CHLORHEXIDINE GLUCONATE; POLYOXYL 40 HYDROGENATED CASTOR OIL; GLYCERIN; BENZETHONIUM CHLORIDE; WATER

76860-006

NA

Active Ingredient(s)

Benzalkonium Chloride 0.13%

Purpose

Antibacterial Agent

Use

for hand-washing to decrease bacteria on the skin, only when water is not available

Warnings

For external use only

WHEN USING

When using the product do not get into eyes. If contact occurs, rinse thoroughly with water.

Stop use and ask a doctor if irritation occurs or rash develops and continues for more than 72 hours.

Keep out of reach of children. If swallowed, get medical help or contact a Poison Control Center right away.

Directions

adults and children 2 years and over

- apply to hands

- allow skin to dry without wiping

children under 2 years

ask a doctor before use

Inactive ingredients

Water, Glycerin, PEG-40 Hydrogenated Castor Oil, Chlorhexidine Digluconate, Benzethonium Chloride, Fragrance (Parfum).